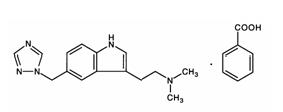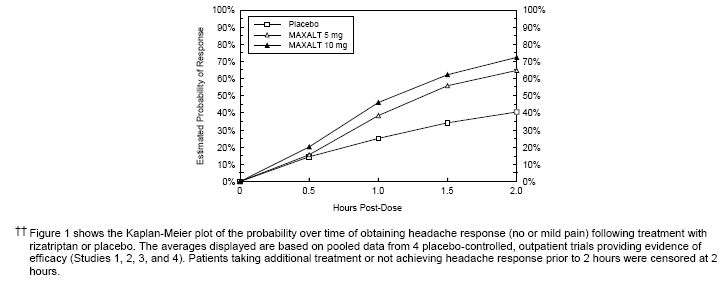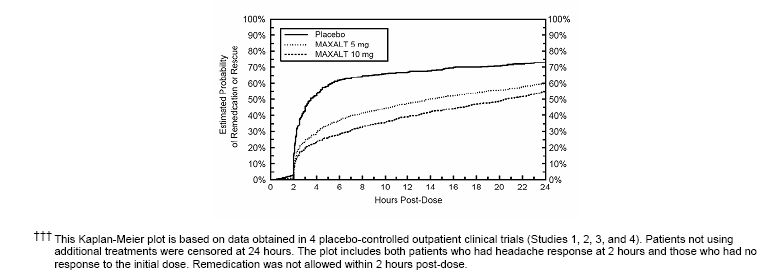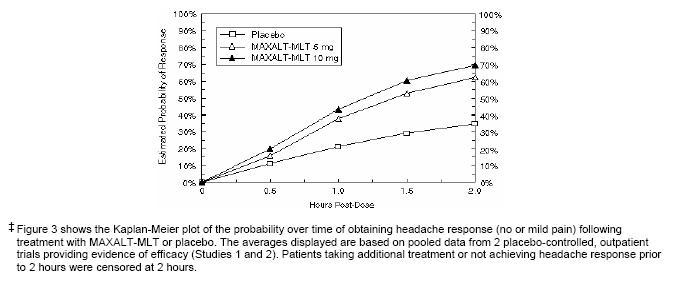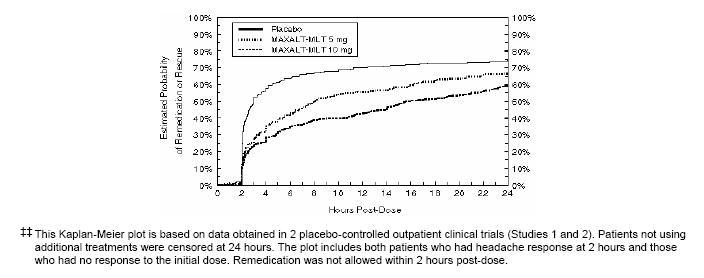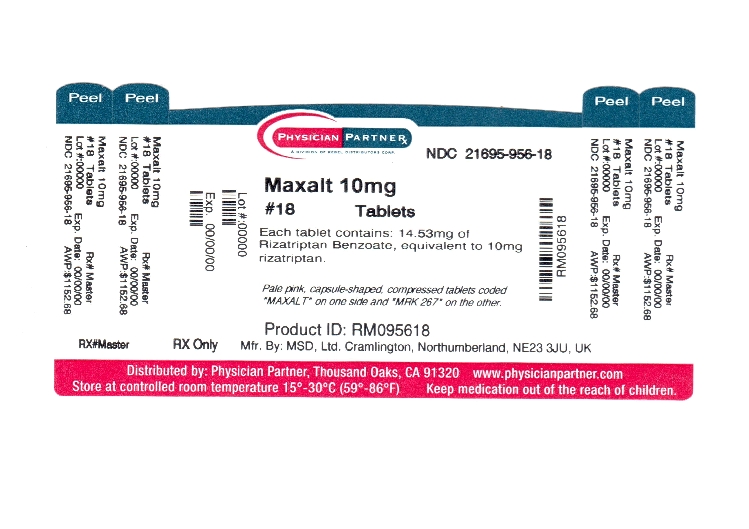 DRUG LABEL: MAXALT
NDC: 21695-956 | Form: TABLET
Manufacturer: Rebel Distributors Corp
Category: prescription | Type: HUMAN PRESCRIPTION DRUG LABEL
Date: 20110913

ACTIVE INGREDIENTS: rizatriptan benzoate 10 mg/1 1
INACTIVE INGREDIENTS: lactose monohydrate; CELLULOSE, MICROCRYSTALLINE; STARCH, CORN; FERRIC OXIDE RED; magnesium stearate

MAXALT®
(RIZATRIPTAN BENZOATE)
TABLETS
MAXALT-MLT®
(RIZATRIPTAN BENZOATE)
ORALLY DISINTEGRATING TABLETS

DESCRIPTION

MAXALT [COPYRIGHT © 1998, 2006 Merck Sharp & Dohme Corp., a subsidiary of Merck & Co., Inc. All rights reserved] contains rizatriptan benzoate, a selective 5-hydroxytryptamine1B/1D (5-HT1B/1D) receptor agonist.

Rizatriptan benzoate is described chemically as: N,N-dimethyl-5-(1H-1,2,4-triazol-1-ylmethyl)-1H-indole-3-ethanamine monobenzoate and its structural formula is:

Its empirical formula is C15H19N5•C7H6O2, representing a molecular weight of the free base of 269.4. Rizatriptan benzoate is a white to off-white, crystalline solid that is soluble in water at about 42 mg per mL (expressed as free base) at 25°C.

MAXALT Tablets and MAXALT-MLT [COPYRIGHT © 1998, 2006 Merck Sharp & Dohme Corp., a subsidiary of Merck & Co., Inc. All rights reserved] Orally Disintegrating Tablets are available for oral administration in strengths of 5 and 10 mg (corresponding to 7.265 mg or 14.53 mg of the benzoate salt, respectively). Each compressed tablet contains the following inactive ingredients: lactose monohydrate, microcrystalline cellulose, pregelatinized starch, ferric oxide (red), and magnesium stearate.

Each lyophilized orally disintegrating tablet contains the following inactive ingredients: gelatin, mannitol, glycine, aspartame, and peppermint flavor.

CLINICAL PHARMACOLOGY

Mechanism of Action

Rizatriptan binds with high affinity to human cloned 5-HT1B and 5-HT1D receptors. Rizatriptan has weak affinity for other 5-HT1 receptor subtypes (5-HT1A, 5-HT1E, 5-HT1F) and the 5-HT7 receptor, but has no significant activity at 5-HT2, 5-HT3, alpha- and beta-adrenergic, dopaminergic, histaminergic, muscarinic or benzodiazepine receptors.

Current theories on the etiology of migraine headache suggest that symptoms are due to local cranial vasodilatation and/or to the release of vasoactive and pro-inflammatory peptides from sensory nerve endings in an activated trigeminal system. The therapeutic activity of rizatriptan in migraine can most likely be attributed to agonist effects at 5-HT1B/1D receptors on the extracerebral, intracranial blood vessels that become dilated during a migraine attack and on nerve terminals in the trigeminal system. Activation of these receptors results in cranial vessel constriction, inhibition of neuropeptide release and reduced transmission in trigeminal pain pathways.

Pharmacokinetics

Rizatriptan is completely absorbed following oral administration. The mean oral absolute bioavailability of the MAXALT Tablet is about 45%, and mean peak plasma concentrations (Cmax) are reached in approximately 1-1.5 hours (Tmax). The presence of a migraine headache did not appear to affect the absorption or pharmacokinetics of rizatriptan. Food has no significant effect on the bioavailability of rizatriptan but delays the time to reach peak concentration by an hour. In clinical trials, MAXALT was administered without regard to food. The plasma half-life of rizatriptan in males and females averages 2-3 hours.

The bioavailability and Cmax of rizatriptan were similar following administration of MAXALT Tablets and MAXALT-MLT Orally Disintegrating Tablets, but the rate of absorption is somewhat slower with MAXALT-MLT, with Tmax averaging 1.6-2.5 hours. AUC of rizatriptan is approximately 30% higher in females than in males. No accumulation occurred on multiple dosing.

The mean volume of distribution is approximately 140 liters in male subjects and 110 liters in female subjects. Rizatriptan is minimally bound (14%) to plasma proteins.

The primary route of rizatriptan metabolism is via oxidative deamination by monoamine oxidase-A (MAO-A) to the indole acetic acid metabolite, which is not active at the 5-HT1B/1D receptor. N-monodesmethyl-rizatriptan, a metabolite with activity similar to that of parent compound at the 5-HT1B/1D receptor, is formed to a minor degree. Plasma concentrations of N-monodesmethyl-rizatriptan are approximately 14% of those of parent compound, and it is eliminated at a similar rate. Other minor metabolites, the N-oxide, the 6-hydroxy compound, and the sulfate conjugate of the 6-hydroxy metabolite are not active at the 5-HT1B/1D receptor.

The total radioactivity of the administered dose recovered over 120 hours in urine and feces was 82% and 12%, respectively, following a single 10 mg oral administration of ^14C-rizatriptan. Following oral administration of ^14C-rizatriptan, rizatriptan accounted for about 17% of circulating plasma radioactivity. Approximately 14% of an oral dose is excreted in urine as unchanged rizatriptan while 51% is excreted as indole acetic acid metabolite, indicating substantial first pass metabolism.

Cytochrome P450 Isoforms: Rizatriptan is not an inhibitor of the activities of human liver cytochrome P450 isoforms 3A4/5, 1A2, 2C9, 2C19, or 2E1; rizatriptan is a competitive inhibitor (Ki=1400 nM) of cytochrome P450 2D6, but only at high, clinically irrelevant concentrations.

Special Populations

Age: Rizatriptan pharmacokinetics in healthy elderly non-migraineur volunteers (age 65-77 years) were similar to those in younger non-migraineur volunteers (age 18-45 years).

Gender: The mean AUC0-∞ and Cmax of rizatriptan (10 mg orally) were about 30% and 11% higher in females as compared to males, respectively, while Tmax occurred at approximately the same time.

Hepatic impairment: Following oral administration in patients with hepatic impairment caused by mild to moderate alcoholic cirrhosis of the liver, plasma concentrations of rizatriptan were similar in patients with mild hepatic insufficiency compared to a control group of healthy subjects; plasma concentrations of rizatriptan were approximately 30% greater in patients with moderate hepatic insufficiency. (See PRECAUTIONS.)

Renal impairment: In patients with renal impairment (creatinine clearance 10-60 mL/min/1.73 m^2), the AUC0-∞ of rizatriptan was not significantly different from that in healthy subjects. In hemodialysis patients, (creatinine clearance < 2 mL/min/1.73 m^2), however, the AUC for rizatriptan was approximately 44% greater than that in patients with normal renal function. (See PRECAUTIONS.)

Race: Pharmacokinetic data revealed no significant differences between African American and Caucasian subjects.

Drug Interactions

(See also PRECAUTIONS, Drug Interactions.)

Monoamine oxidase inhibitors: Rizatriptan is principally metabolized via monoamine oxidase, ‘A’ subtype (MAO-A). Plasma concentrations of rizatriptan may be increased by drugs that are selective MAO-A inhibitors (e.g., moclobemide) or nonselective MAO inhibitors [type A and B] (e.g., isocarboxazid, phenelzine, tranylcypromine, and pargyline). In a drug interaction study, when MAXALT 10 mg was administered to subjects (n=12) receiving concomitant therapy with the selective, reversible MAO-A inhibitor, moclobemide 150 mg t.i.d., there were mean increases in rizatriptan AUC and Cmax of 119% and 41% respectively; and the AUC of the active N-monodesmethyl metabolite of rizatriptan was increased more than 400%. The interaction would be expected to be greater with irreversible MAO inhibitors. No pharmacokinetic interaction is anticipated in patients receiving selective MAO-B inhibitors. (See CONTRAINDICATIONS; PRECAUTIONS, Drug Interactions.)

Propranolol: In a study of concurrent administration of propranolol 240 mg/day and a single dose of rizatriptan 10 mg in healthy subjects (n=11), mean plasma AUC for rizatriptan was increased by 70% during propranolol administration, and a fourfold increase was observed in one subject. The AUC of the active N-monodesmethyl metabolite of rizatriptan was not affected by propranolol. (See PRECAUTIONS; DOSAGE AND ADMINISTRATION.)

Nadolol/Metoprolol: In a drug interactions study, effects of multiple doses of nadolol 80 mg or metoprolol 100 mg every 12 hours on the pharmacokinetics of a single dose of 10 mg rizatriptan were evaluated in healthy subjects (n=12). No pharmacokinetic interactions were observed.

Paroxetine: In a study of the interaction between the selective serotonin reuptake inhibitor (SSRI) paroxetine 20 mg/day for two weeks and a single dose of MAXALT 10 mg in healthy subjects (n=12), neither the plasma concentrations of rizatriptan nor its safety profile were affected by paroxetine (see WARNINGS and PRECAUTIONS, Information for Patients).

Oral contraceptives: In a study of concurrent administration of an oral contraceptive during 6 days of administration of MAXALT (10-30 mg/day) in healthy female volunteers (n=18), rizatriptan did not affect plasma concentrations of ethinyl estradiol or norethindrone.

Clinical Studies

The efficacy of MAXALT Tablets was established in four multicenter, randomized, placebo-controlled trials. Patients enrolled in these studies were primarily female (84%) and Caucasian (88%), with a mean age of 40 years (range of 18 to 71). Patients were instructed to treat a moderate to severe headache. Headache response, defined as a reduction of moderate or severe headache pain to no or mild headache pain, was assessed for up to 2 hours (Study 1) or up to 4 hours after dosing (Studies 2, 3 and 4). Associated symptoms of nausea, photophobia, and phonophobia and maintenance of response up to 24 hours postdose were evaluated. A second dose of MAXALT Tablets was allowed 2 to 24 hours after dosing for treatment of recurrent headache in Studies 1 and 2. Additional analgesics and/or antiemetics were allowed 2 hours after initial treatment for rescue in all four studies.

In all studies, the percentage of patients achieving headache response 2 hours after treatment was significantly greater in patients who received either MAXALT 5 or 10 mg compared to those who received placebo. In a separate study, doses of 2.5 mg were not different from placebo. Doses greater than 10 mg were associated with an increased incidence of adverse effects. The results from the 4 controlled studies using the marketed formulation are summarized in Table 1.

Table 1: Response Rates 2 Hours Following Treatment of Initial Headache
Study | Placebo | MAXALT Tablets 5 mg | MAXALT Tablets 10 mg
1 | 35% (n=304) | 62% [p value < 0.05 in comparison with placebo] (n=458) | 71%, [p value < 0.05 in comparison with 5 mg] (n=456)
2 [Results for initial headache only.] | 37% (n=82) | — | 77% (n=320)
3 | 23% (n=80) | 63% (n=352) | —
4 | 40% (n=159) | 60% (n=164) | 67% (n=385)

Comparisons of drug performance based upon results obtained in different clinical trials are never reliable. Because studies are conducted at different times, with different samples of patients, by different investigators, employing different criteria and/or different interpretations of the same criteria, under different conditions (dose, dosing regimen, etc.), quantitative estimates of treatment response and the timing of response may be expected to vary considerably from study to study.

The estimated probability of achieving an initial headache response within 2 hours following treatment is depicted in Figure 1.

Figure 1: Estimated Probability of Achieving an Initial Headache Response by 2 Hours††

For patients with migraine-associated photophobia, phonophobia, and nausea at baseline, there was a decreased incidence of these symptoms following administration of MAXALT compared to placebo.

Two to 24 hours following the initial dose of study treatment, patients were allowed to use additional treatment for pain response in the form of a second dose of study treatment or other medication. The estimated probability of patients taking a second dose or other medication for migraine over the 24 hours following the initial dose of study treatment is summarized in Figure 2.

Figure 2: Estimated Probability of Patients Taking a Second Dose of MAXALT Tablets or Other Medication for Migraines Over the 24 Hours Following the Initial Dose of Study Treatment†††

Efficacy was unaffected by the presence of aura; by the gender, or age of the patient; or by concomitant use of common migraine prophylactic drugs (e.g., beta-blockers, calcium channel blockers, tricyclic antidepressants) or oral contraceptives. In two additional similar studies, efficacy was unaffected by relationship to menses. There were insufficient data to assess the impact of race on efficacy.

In a single study in adolescents (n=291), there were no statistically significant differences between treatment groups. The headache response rates at 2 hours were 66% and 56% for MAXALT 5 mg Tablets and placebo, respectively.

MAXALT-MLT Orally Disintegrating Tablets

The efficacy of MAXALT-MLT was established in two multicenter, randomized, placebo-controlled trials that were similar in design to the trials of MAXALT Tablets. Patients were instructed to treat a moderate to severe headache. Patients treated in these studies were primarily female (88%) and Caucasian (95%), with a mean age of 42 years (range 18-72).

In both studies, the percentage of patients achieving headache response 2 hours after treatment was significantly greater in patients who received either MAXALT-MLT 5 or 10 mg compared to those who received placebo. The results from the 2 controlled studies using the marketed formulation are summarized in Table 2.

Table 2: Response Rates 2 Hours Following Treatment of Initial Headache
Study | Placebo | MAXALT-MLT 5 mg | MAXALT-MLT 10 mg
1 | 47% (n=98) | 66% [p value < 0.01 in comparison with placebo] (n=100) | 66% (n=113)
2 | 28% (n=180) | 59% (n=181) | 74%, [p value < 0.01 in comparison with 5 mg] (n=186)

The estimated probability of achieving an initial headache response by 2 hours following treatment with MAXALT-MLT is depicted in Figure 3.

Figure 3: Estimated Probability of Achieving an Initial Headache Response with MAXALT-MLT by 2 Hours‡

For patients with migraine-associated photophobia and phonophobia at baseline, there was a decreased incidence of these symptoms following administration of MAXALT-MLT as compared to placebo.

Two to 24 hours following the initial dose of study treatment, patients were allowed to use additional treatment for pain response in the form of a second dose of study treatment or other medication. The estimated probability of patients taking a second dose or other medication for migraine over the 24 hours following the initial dose of study treatment is summarized in Figure 4.

Figure 4: Estimated Probability of Patients Taking a Second Dose of MAXALT-MLT or Other Medication for Migraines Over the 24 Hours Following the Initial Dose of Study Treatment‡‡

INDICATIONS AND USAGE

MAXALT is indicated for the acute treatment of migraine attacks with or without aura in adults.

MAXALT is not intended for the prophylactic therapy of migraine or for use in the management of hemiplegic or basilar migraine (see CONTRAINDICATIONS). Safety and effectiveness of MAXALT have not been established for cluster headache, which is present in an older, predominantly male population.

CONTRAINDICATIONS

MAXALT should not be given to patients with ischemic heart disease (e.g., angina pectoris, history of myocardial infarction, or documented silent ischemia) or to patients who have symptoms or findings consistent with ischemic heart disease, coronary artery vasospasm, including Prinzmetal’s variant angina, or other significant underlying cardiovascular disease (see WARNINGS).

Because MAXALT may increase blood pressure, it should not be given to patients with uncontrolled hypertension (see WARNINGS).

MAXALT should not be used within 24 hours of treatment with another 5-HT1 agonist, or an ergotamine-containing or ergot-type medication like dihydroergotamine or methysergide.

MAXALT should not be administered to patients with hemiplegic or basilar migraine.

Concurrent administration of MAO inhibitors or use of rizatriptan within 2 weeks of discontinuation of MAO inhibitor therapy is contraindicated (see CLINICAL PHARMACOLOGY, Drug Interactions and PRECAUTIONS, Drug Interactions).

MAXALT is contraindicated in patients who are hypersensitive to rizatriptan or any of its inactive ingredients.

WARNINGS

MAXALT should only be used where a clear diagnosis of migraine has been established.

Risk of Myocardial Ischemia and/or Infarction and Other Adverse Cardiac Events: Because of the potential of this class of compounds (5-HT1B/1D agonists) to cause coronary vasospasm, MAXALT should not be given to patients with documented ischemic or vasospastic coronary artery disease (see CONTRAINDICATIONS). It is strongly recommended that rizatriptan not be given to patients in whom unrecognized coronary artery disease (CAD) is predicted by the presence of risk factors (e.g., hypertension, hypercholesterolemia, smoker, obesity, diabetes, strong family history of CAD, female with surgical or physiological menopause, or male over 40 years of age) unless a cardiovascular evaluation provides satisfactory clinical evidence that the patient is reasonably free of coronary artery and ischemic myocardial disease or other significant underlying cardiovascular disease. The sensitivity of cardiac diagnostic procedures to detect cardiovascular disease or predisposition to coronary artery vasospasm is modest, at best. If, during the cardiovascular evaluation, the patient’s medical history, electrocardiographic or other investigations reveal findings indicative of, or consistent with, coronary artery vasospasm or myocardial ischemia, rizatriptan should not be administered (see CONTRAINDICATIONS).

For patients with risk factors predictive of CAD, who are determined to have a satisfactory cardiovascular evaluation, it is strongly recommended that administration of the first dose of rizatriptan take place in the setting of a physician’s office or similar medically staffed and equipped facility unless the patient has previously received rizatriptan. Because cardiac ischemia can occur in the absence of clinical symptoms, consideration should be given to obtaining on the first occasion of use an electrocardiogram (ECG) during the interval immediately following MAXALT, in these patients with risk factors.

It is recommended that patients who are intermittent long-term users of MAXALT and who have or acquire risk factors predictive of CAD, as described above, undergo periodic interval cardiovascular evaluation as they continue to use MAXALT.

The systematic approach described above is intended to reduce the likelihood that patients with unrecognized cardiovascular disease will be inadvertently exposed to rizatriptan.

Cardiac Events and Fatalities Associated with 5-HT1 Agonists: Serious adverse cardiac events, including acute myocardial infarction, have been reported within a few hours following the administration of rizatriptan. Life-threatening disturbances of cardiac rhythm and death have been reported within a few hours following the administration of other 5-HT1 agonists. Considering the extent of use of 5-HT1 agonists in patients with migraine, the incidence of these events is extremely low. MAXALT can cause coronary vasospasm. Because of the close proximity of the events to MAXALT use, a causal relationship cannot be excluded. In the cases where there has been known underlying coronary artery disease, the relationship is uncertain.

Premarketing experience with rizatriptan: Among the 3700 patients with migraine who participated in premarketing clinical trials of MAXALT, one patient was reported to have chest pain with possible ischemic ECG changes following a single dose of 10 mg.

Postmarketing experience with rizatriptan: Serious cardiovascular events have been reported in association with the use of MAXALT. The uncontrolled nature of postmarketing surveillance, however, makes it impossible to determine definitively the proportion of the reported cases that were actually caused by rizatriptan or to reliably assess causation in individual cases.

Cerebrovascular Events and Fatalities Associated with 5-HT1 Agonists: Cerebral hemorrhage, subarachnoid hemorrhage, stroke, and other cerebrovascular events have been reported in patients treated with 5-HT1 agonists; and some have resulted in fatalities. In a number of cases, it appears possible that the cerebrovascular events were primary, the agonist having been administered in the incorrect belief that the symptoms experienced were a consequence of migraine, when they were not. It should be noted that patients with migraine may be at increased risk of certain cerebrovascular events (e.g., stroke, hemorrhage, transient ischemic attack).

Other Vasospasm-Related Events: 5-HT1 agonists may cause vasospastic reactions other than coronary artery vasospasm. Both peripheral vascular ischemia and colonic ischemia with abdominal pain and bloody diarrhea have been reported with 5-HT1 agonists.

Increase in Blood Pressure: Significant elevation in blood pressure, including hypertensive crisis, has been reported on rare occasions in patients receiving 5-HT1 agonists with and without a history of hypertension. In healthy young male and female subjects who received maximal doses of MAXALT (10 mg every 2 hours for 3 doses), slight increases in blood pressure (approximately 2-3 mmHg) were observed. Rizatriptan is contraindicated in patients with uncontrolled hypertension (see CONTRAINDICATIONS).

An 18% increase in mean pulmonary artery pressure was seen following dosing with another 5-HT1 agonist in a study evaluating subjects undergoing cardiac catheterization.

Serotonin Syndrome: The development of a potentially life-threatening serotonin syndrome may occur with triptans, including MAXALT treatment, particularly during combined use with selective serotonin reuptake inhibitors (SSRIs) or serotonin norepinephrine reuptake inhibitors (SNRIs). If concomitant treatment with rizatriptan and an SSRI (e.g., fluoxetine, paroxetine, sertraline, fluvoxamine, citalopram, escitalopram) or SNRI (e.g., venlafaxine, duloxetine) is clinically warranted, careful observation of the patient is advised, particularly during treatment initiation and dose increases. Serotonin syndrome symptoms may include mental status changes (e.g., agitation, hallucinations, coma), autonomic instability (e.g., tachycardia, labile blood pressure, hyperthermia), neuromuscular aberrations (e.g., hyperreflexia, incoordination) and/or gastrointestinal symptoms (e.g., nausea, vomiting, diarrhea) (see PRECAUTIONS, Drug Interactions).

PRECAUTIONS

General

As with other 5-HT1B/1D agonists, sensations of tightness, pain, pressure, and heaviness have been reported after treatment with MAXALT in the precordium, throat, neck and jaw. These events have not been associated with arrhythmias or definite ischemic ECG changes in clinical trials (one patient experienced chest pain with possible ischemic ECG changes). Because drugs in this class may cause coronary artery vasospasm, patients who experience signs or symptoms suggestive of angina following dosing should be evaluated for the presence of CAD or a predisposition to Prinzmetal’s variant angina before receiving additional doses of medication, and should be monitored electrocardiographically if dosing is resumed and similar symptoms recur. Similarly, patients who experience other symptoms or signs suggestive of decreased arterial flow, such as ischemic bowel syndrome or Raynaud’s syndrome following the use of any 5-HT1 agonist are candidates for further evaluation (see WARNINGS).

Rizatriptan should also be administered with caution to patients with diseases that may alter the absorption, metabolism, or excretion of drugs (see CLINICAL PHARMACOLOGY, Special Populations).

Renally Impaired Patients: Rizatriptan should be used with caution in dialysis patients due to a decrease in the clearance of rizatriptan (see CLINICAL PHARMACOLOGY, Special Populations).

Hepatically Impaired Patients: Rizatriptan should be used with caution in patients with moderate hepatic insufficiency due to an increase in plasma concentrations of approximately 30% (see CLINICAL PHARMACOLOGY, Special Populations).

For a given attack, if a patient has no response to the first dose of rizatriptan, the diagnosis of migraine should be reconsidered before administration of a second dose.

Binding to Melanin-Containing Tissues

The propensity for rizatriptan to bind melanin has not been investigated. Based on its chemical properties, rizatriptan may bind to melanin and accumulate in melanin rich tissue (e.g., eye) over time. This raises the possibility that rizatriptan could cause toxicity in these tissues after extended use. There were, however, no adverse ophthalmologic changes related to treatment with rizatriptan in the one year dog toxicity study. Although no systematic monitoring of ophthalmologic function was undertaken in clinical trials, and no specific recommendations for ophthalmologic monitoring are offered, prescribers should be aware of the possibility of long-term ophthalmologic effects.

Phenylketonurics

Phenylketonuric patients should be informed that MAXALT-MLT Orally Disintegrating Tablets contain phenylalanine (a component of aspartame). Each 5-mg orally disintegrating tablet contains 1.05 mg phenylalanine, and each 10-mg orally disintegrating tablet contains 2.10 mg phenylalanine.

Information for Patients

Migraine or treatment with MAXALT may cause somnolence in some patients. Dizziness has also been reported in some patients receiving MAXALT. Patients should, therefore, evaluate their ability to perform complex tasks during migraine attacks and after administration of MAXALT.

Physicians should instruct their patients to read the patient package insert before taking MAXALT. See the accompanying PATIENT INFORMATION leaflet.

Patients should be cautioned about the risk of serotonin syndrome with the use of rizatriptan or other triptans, especially during combined use with selective serotonin reuptake inhibitors (SSRIs) or serotonin norepinephrine reuptake inhibitors (SNRIs) (see WARNINGS).

MAXALT-MLT Orally Disintegrating Tablets

Patients should be instructed not to remove the blister from the outer pouch until just prior to dosing. The blister pack should then be peeled open with dry hands and the orally disintegrating tablet placed on the tongue, where it will dissolve and be swallowed with the saliva.

Laboratory Tests

No specific laboratory tests are recommended for monitoring patients prior to and/or after treatment with MAXALT.

Drug Interactions

(See also CLINICAL PHARMACOLOGY, Drug Interactions.)

Propranolol: Rizatriptan 5 mg should be used in patients taking propranolol, as propranolol has been shown to increase the plasma concentrations of rizatriptan by 70% (see CLINICAL PHARMACOLOGY, Drug Interactions; DOSAGE AND ADMINISTRATION).

Ergot-containing drugs: Ergot-containing drugs have been reported to cause prolonged vasospastic reactions. Because there is a theoretical basis that these effects may be additive, use of ergotamine-containing or ergot-type medications (like dihydroergotamine or methysergide) and rizatriptan within 24 hours is contraindicated (see CONTRAINDICATIONS).

Other 5-HT1 agonists: The administration of rizatriptan with other 5-HT1 agonists has not been evaluated in migraine patients. Because their vasospastic effects may be additive, coadministration of rizatriptan and other 5-HT1 agonists within 24 hours of each other is not recommended (see CONTRAINDICATIONS).

Selective Serotonin Reuptake Inhibitors/Serotonin Norepinephrine Reuptake Inhibitors and Serotonin Syndrome: Cases of life-threatening serotonin syndrome have been reported during combined use of selective serotonin reuptake inhibitors (SSRIs) or serotonin norepinephrine reuptake inhibitors (SNRIs) and triptans (see WARNINGS).

Monoamine oxidase inhibitors: Rizatriptan should not be administered to patients taking MAO-A inhibitors and non-selective MAO inhibitors; it has been shown that moclobemide (a specific MAO-A inhibitor) increased the systemic exposure of rizatriptan and its metabolite (see CLINICAL PHARMACOLOGY, Drug Interactions; CONTRAINDICATIONS).

Drug/Laboratory Test Interactions

MAXALT is not known to interfere with commonly employed clinical laboratory tests.

Carcinogenesis, Mutagenesis, Impairment of Fertility

Carcinogenesis: The lifetime carcinogenic potential of rizatriptan was evaluated in a 100-week study in mice and a 106-week study in rats at oral gavage doses of up to 125 mg/kg/day. Exposure data were not obtained in those studies, but plasma AUC’s of parent drug measured in other studies after 5 and 21 weeks of oral dosing in mice and rats, respectively, indicate that the exposures to parent drug at the highest dose level in the carcinogenicity studies would have been approximately 150 times (mice) and 240 times (rats) average AUC’s measured in humans after three 10 mg doses, the maximum recommended total daily dose. There was no evidence of an increase in tumor incidence related to rizatriptan in either species.

Mutagenesis: Rizatriptan, with and without metabolic activation, was neither mutagenic, nor clastogenic in a battery of in vitro and in vivo genetic toxicity studies, including: the microbial mutagenesis (Ames) assay, the in vitro mammalian cell mutagenesis assay in V-79 Chinese hamster lung cells, the in vitro alkaline elution assay in rat hepatocytes, the in vitro chromosomal aberration assay in Chinese hamster ovary cells and the in vivo chromosomal aberration assay in mouse bone marrow.

Impairment of Fertility: In a fertility study in rats, altered estrus cyclicity and delays in time to mating were observed in females treated orally with 100 mg/kg/day rizatriptan. Plasma drug exposure (AUC) at this dose was approximately 225 times the exposure in humans receiving the maximum recommended daily dose (MRDD) of 30 mg. The no-effect dose was 10 mg/kg/day (approximately 15 times the human exposure at the MRDD). There were no other fertility-related effects in the female rats. There was no impairment of fertility or reproductive performance in male rats treated with up to 250 mg/kg/day (approximately 550 times the human exposure at the MRDD).

Pregnancy:

Pregnancy Category C

In a general reproductive study in rats, birth weights and pre- and post-weaning weight gain were reduced in the offspring of females treated prior to and during mating and throughout gestation and lactation with doses of 10 and 100 mg/kg/day. Maternal drug exposures (AUC) at these doses were approximately 15 and 225 times, respectively, the exposure in humans receiving the maximum recommended daily dose (MRDD) of 30 mg. In a pre- and post-natal developmental toxicity study in rats, an increase in mortality of the offspring at birth and for the first three days after birth, a decrease in pre- and post-weaning weight gain, and decreased performance in a passive avoidance test (which indicates a decrease in learning capacity of the offspring) were observed at doses of 100 and 250 mg/kg/day. The no-effect dose for all of these effects was 5 mg/kg/day, approximately 7.5 times the exposure in humans receiving the MRDD. With doses of 100 and 250 mg/kg/day, the decreases in average weight of both the male and female offspring persisted into adulthood. All of these effects on the offspring in both reproductive toxicity studies occurred in the absence of any apparent maternal toxicity.

In embryofetal development studies, no teratogenic effects were observed when pregnant rats and rabbits were administered doses of 100 and 50 mg/kg/day, respectively, during organogenesis. Fetal weights were decreased in conjunction with decreased maternal weight gain at the highest doses (maternal exposures approximately 225 and 115 times the human exposure at the MRDD in rats and rabbits, respectively). The developmental no-effect dose in these studies was 10 mg/kg/day in both rats and rabbits (maternal exposures approximately 15 times human exposure at the MRDD). Toxicokinetic studies demonstrated placental transfer of drug in both species.

There are no adequate and well-controlled studies in pregnant women; therefore, rizatriptan should be used during pregnancy only if the potential benefit justifies the potential risk to the fetus.

Merck Sharp & Dohme Corp., a subsidiary of Merck & Co., Inc., maintains a registry to monitor the pregnancy outcomes of women exposed to MAXALT while pregnant. Healthcare providers are encouraged to report any prenatal exposure to MAXALT by calling the Pregnancy Registry at (800) 986-8999.

Nursing Mothers

It is not known whether this drug is excreted in human milk. Because many drugs are excreted in human milk, caution should be exercised when MAXALT is administered to women who are breast-feeding. Rizatriptan is extensively excreted in rat milk, at a level of 5-fold or greater than maternal plasma levels.

Pediatric Use

Safety and effectiveness of rizatriptan in pediatric patients have not been established; therefore, MAXALT is not recommended for use in patients under 18 years of age.

The efficacy of MAXALT Tablets (5 mg) in patients aged 12 to 17 years was not established in a randomized placebo-controlled trial of 291 adolescent migraineurs (see Clinical Studies). Adverse events observed were similar in nature to those reported in clinical trials in adults. Postmarketing experience with other triptans includes a limited number of reports that describe pediatric patients who have experienced clinically serious adverse events that are similar in nature to those reported rarely in adults. The long-term safety of rizatriptan in pediatric patients has not been studied.

Geriatric Use

The pharmacokinetics of rizatriptan were similar in elderly (aged ≥ 65 years) and in younger adults. Because migraine occurs infrequently in the elderly, clinical experience with MAXALT is limited in such patients. In clinical trials, there were no apparent differences in efficacy or in overall adverse experience rates between patients under 65 years of age and those 65 and above (n=17).

ADVERSE REACTIONS

Serious cardiac events, including some that have been fatal, have occurred following use of 5-HT1 agonists. These events are extremely rare and most have been reported in patients with risk factors predictive of CAD. Events reported have included coronary artery vasospasm, transient myocardial ischemia, myocardial infarction, ventricular tachycardia, and ventricular fibrillation (see CONTRAINDICATIONS, WARNINGS, and PRECAUTIONS).

Incidence in Controlled Clinical Trials: Adverse experiences to rizatriptan were assessed in controlled clinical trials that included over 3700 patients who received single or multiple doses of MAXALT Tablets. The most common adverse events during treatment with MAXALT were asthenia/fatigue, somnolence, pain/pressure sensation and dizziness. These events appeared to be dose related. In long term extension studies where patients were allowed to treat multiple attacks for up to 1 year, 4% (59 out of 1525 patients) withdrew because of adverse experiences.

Table 3 lists the adverse events regardless of drug relationship (incidence ≥ 2% and greater than placebo) after a single dose of MAXALT. The events cited reflect experience gained under closely monitored conditions of clinical trials in a highly selected patient population. In actual clinical practice or in other clinical trials, these frequency estimates may not apply, as the conditions of use, reporting behavior, and the kinds of patients treated may differ.

Table 3: Incidence (≥ 2% and Greater than Placebo) of Adverse Experiences After a Single Dose of MAXALT Tablets or Placebo
 | % of Patients
Adverse Experiences | MAXALT 5 mg (N=977) | MAXALT 10 mg (N=1167) | Placebo (N=627)
Atypical Sensations | 4 | 5 | 4
Paresthesia | 3 | 4 | <2
Pain and other Pressure Sensations | 6 | 9 | 3
Chest Pain: tightness/pressure and/or heaviness | <2 | 3 | 1
Neck/throat/jaw: pain/tightness/pressure | <2 | 2 | 1
Regional Pain: tightness/pressure/heaviness | <1 | 2 | 0
Pain, location unspecified | 3 | 3 | <2
Digestive | 9 | 13 | 8
Dry Mouth | 3 | 3 | 1
Nausea | 4 | 6 | 4
Neurological | 14 | 20 | 11
Dizziness | 4 | 9 | 5
Headache | <2 | 2 | <1
Somnolence | 4 | 8 | 4
Other Asthenia/fatigue | 4 | 7 | 2

MAXALT was generally well-tolerated. Adverse experiences were typically mild in intensity and were transient. The frequencies of adverse experiences in clinical trials did not increase when up to three doses were taken within 24 hours. Adverse event frequencies were also unchanged by concomitant use of drugs commonly taken for migraine prophylaxis (including propranolol), oral contraceptives, or analgesics. The incidences of adverse experiences were not affected by age or gender. There were insufficient data to assess the impact of race on the incidence of adverse events.

Other Events Observed in Association with the Administration of MAXALT: In the section that follows, the frequencies of less commonly reported adverse clinical events are presented. Because the reports include events observed in open studies, the role of MAXALT in their causation cannot be reliably determined. Furthermore, variability associated with adverse event reporting, the terminology used to describe adverse events, etc., limit the value of the quantitative frequency estimates provided. Event frequencies are calculated as the number of patients who used MAXALT (N=3716) and reported an event divided by the total number of patients exposed to MAXALT. All reported events are included, except those already listed in the previous table, those too general to be informative, and those not reasonably associated with the use of the drug. Events are further classified within body system categories and enumerated in order of decreasing frequency using the following definitions: frequent adverse events are those defined as those occurring in at least (>)1/100 patients; infrequent adverse experiences are those occurring in 1/100 to 1/1000 patients; and rare adverse experiences are those occurring in fewer than 1/1000 patients.

General: Infrequent were chills, heat sensitivity, facial edema, hangover effect, and abdominal distention. Rare were fever, orthostatic effects, syncope and edema/swelling.

Atypical Sensations: Frequent were warm/cold sensations.

Cardiovascular: Frequent was palpitation. Infrequent were tachycardia, cold extremities, hypertension, arrhythmia, and bradycardia. Rare was angina pectoris.

Digestive: Frequent were diarrhea and vomiting. Infrequent were dyspepsia, thirst, acid regurgitation, dysphagia, constipation, flatulence, and tongue edema. Rare were anorexia, appetite increase, gastritis, paralysis (tongue), and eructation.

Metabolic: Infrequent was dehydration.

Musculoskeletal: Infrequent were muscle weakness, stiffness, myalgia, muscle cramp, musculoskeletal pain, arthralgia, and muscle spasm.

Neurological/Psychiatric: Frequent were hypesthesia, mental acuity decreased, euphoria and tremor. Infrequent were nervousness, vertigo, insomnia, anxiety, depression, disorientation, ataxia, dysarthria, confusion, dream abnormality, gait abnormality, irritability, memory impairment, agitation and hyperesthesia. Rare were: dysesthesia, depersonalization, akinesia/bradykinesia, apprehension, hyperkinesia, hypersomnia, and hyporeflexia.

Respiratory: Frequent was dyspnea. Infrequent were pharyngitis, irritation (nasal), congestion (nasal), dry throat, upper respiratory infection, yawning, respiratory congestion (nasal), dry nose, epistaxis, and sinus disorder. Rare were cough, hiccups, hoarseness, rhinorrhea, sneezing, tachypnea, and pharyngeal edema.

Special Senses: Infrequent were blurred vision, tinnitus, dry eyes, burning eye, eye pain, eye irritation, ear pain, and tearing. Rare were hyperacusis, smell perversion, photophobia, photopsia, itching eye, and eye swelling.

Skin and Skin Appendage: Frequent was flushing. Infrequent were sweating, pruritus, rash, and urticaria. Rare were erythema, acne, and photosensitivity.

Urogenital System: Frequent was hot flashes. Infrequent were urinary frequency, polyuria, and menstruation disorder. Rare was dysuria.

The adverse experience profile seen with MAXALT-MLT Orally Disintegrating Tablets was similar to that seen with MAXALT Tablets.

Postmarketing Experience

The following section enumerates potentially important adverse events that have occurred in clinical practice and which have been reported spontaneously to various surveillance systems. The events enumerated represent reports arising from both domestic and non-domestic use of rizatriptan. The events enumerated include all except those already listed in the ADVERSE REACTIONS section above or those too general to be informative. Because the reports cite events reported spontaneously from worldwide postmarketing experience, frequency of events and the role of rizatriptan in their causation cannot be reliably determined.

Cardiovascular: Myocardial ischemia, myocardial infarction, peripheral vascular ischemia (see WARNINGS).

Cerebrovascular: Stroke.

Neurological/Psychiatric: Serotonin syndrome (see WARNINGS), seizure.

Special Senses: Dysgeusia.

General: Hypersensitivity reaction, anaphylaxis/anaphylactoid reaction, angioedema (e.g., facial edema, tongue swelling, pharyngeal edema), wheezing, toxic epidermal necrolysis.

DRUG ABUSE AND DEPENDENCE

Although the abuse potential of MAXALT has not been specifically assessed, no abuse of, tolerance to, withdrawal from, or drug-seeking behavior was observed in patients who received MAXALT in clinical trials or their extensions. The 5-HT1B/1D agonists, as a class, have not been associated with drug abuse.

OVERDOSAGE

No overdoses of MAXALT were reported during clinical trials.

Rizatriptan 40 mg (administered as either a single dose or as two doses with a 2-hour interdose interval) was generally well tolerated in over 300 patients; dizziness and somnolence were the most common drug-related adverse effects.

In a clinical pharmacology study in which 12 subjects received rizatriptan, at total cumulative doses of 80 mg (given within four hours), two subjects experienced syncope and/or bradycardia. One subject, a female aged 29 years, developed vomiting, bradycardia, and dizziness beginning three hours after receiving a total of 80 mg rizatriptan (administered over two hours); a third degree AV block, responsive to atropine, was observed an hour after the onset of the other symptoms. The second subject, a 25 year old male, experienced transient dizziness, syncope, incontinence, and a 5-second systolic pause (on ECG monitor) immediately after a painful venipuncture. The venipuncture occurred two hours after the subject had received a total of 80 mg rizatriptan (administered over four hours).

In addition, based on the pharmacology of rizatriptan, hypertension or other more serious cardiovascular symptoms could occur after overdosage. Gastrointestinal decontamination, (i.e., gastric lavage followed by activated charcoal) should be considered in patients suspected of an overdose with MAXALT. Clinical and electrocardiographic monitoring should be continued for at least 12 hours, even if clinical symptoms are not observed.

The effects of hemo- or peritoneal dialysis on serum concentrations of rizatriptan are unknown.

DOSAGE AND ADMINISTRATION

In controlled clinical trials, single doses of 5 and 10 mg of MAXALT Tablets or MAXALT-MLT were effective for the acute treatment of migraines in adults. There is evidence that the 10-mg dose may provide a greater effect than the 5-mg dose (see CLINICAL PHARMACOLOGY, Clinical Studies). Individuals may vary in response to doses of MAXALT Tablets. The choice of dose should therefore be made on an individual basis, weighing the possible benefit of the 10-mg dose with the potential risk for increased adverse events.

Redosing: Doses should be separated by at least 2 hours; no more than 30 mg should be taken in any 24-hour period.

The safety of treating, on average, more than four headaches in a 30-day period has not been established.

Patients receiving propranolol: In patients receiving propranolol, the 5-mg dose of MAXALT should be used, up to a maximum of 3 doses in any 24-hour period. (See CLINICAL PHARMACOLOGY, Drug Interactions.)

For MAXALT-MLT Orally Disintegrating Tablets, administration with liquid is not necessary. The orally disintegrating tablet is packaged in a blister within an outer aluminum pouch. Patients should be instructed not to remove the blister from the outer pouch until just prior to dosing. The blister pack should then be peeled open with dry hands and the orally disintegrating tablet placed on the tongue, where it will dissolve and be swallowed with the saliva.

HOW SUPPLIED

No. 3733 — MAXALT Tablets, 10 mg, are pale pink, capsule-shaped, compressed tablets coded MAXALT on one side and MRK 267 on the other. They are supplied as follows:

NDC 21695-956-18, carton of 18 tablets.

Storage

Store MAXALT Tablets at room temperature, 15-30°C (59-86°F). Dispense in a tight container, if product is subdivided.

Store MAXALT-MLT Orally Disintegrating Tablets at room temperature, 15-30°C (59-86°F). The patient should be instructed not to remove the blister from the outer aluminum pouch until the patient is ready to consume the orally disintegrating tablet inside.

MAXALT Tablets are manufactured for:
Merck Sharp & Dohme Corp., a subsidiary of
MERCK & CO., INC., Whitehouse Station, NJ 08889, USA

By:
MSD, Ltd.
Cramlington, Northumberland, NE23 3JU, UK

MAXALT-MLT Orally Disintegrating Tablets are manufactured for:
Merck Sharp & Dohme Corp., a subsidiary of
MERCK & CO., INC., Whitehouse Station, NJ 08889, USA

By:
Catalent UK Swindon, Zydis Ltd.
Swindon, Wiltshire, SN5 8RU, UK

US Patent No.: 5,298,520

Issued August 2010

9652508

Repackaged by:

REBEL DISTRIBUTORS CORP

Thousand Oaks, CA 91320

PATIENT PACKAGE INSERT

Patient Information about
MAXALT® (max-awlt) and MAXALT-MLT®
for Migraine
Generic name: rizatriptan benzoate

Please read this information before you start taking MAXALT [COPYRIGHT © 1998, 2006 Merck Sharp & Dohme Corp., a subsidiary of Merck & Co., Inc. All rights reserved] . Also, read the leaflet each time you renew your prescription, just in case anything has changed. Remember, this leaflet does not take the place of careful discussions with your doctor. You and your doctor should discuss MAXALT when you start taking your medication and at regular checkups.

What is MAXALT and what is it used for?

MAXALT is a medication used for the treatment of migraine attacks in adults. MAXALT is a member of a class of drugs called selective 5-HT1B/1D receptor agonists.

It is available as a traditional tablet (MAXALT) and as an orally disintegrating tablet (MAXALT-MLT [COPYRIGHT © 1998, 2006 Merck Sharp & Dohme Corp., a subsidiary of Merck & Co., Inc. All rights reserved]). Unless otherwise stated, the information contained in this leaflet applies both to MAXALT Tablets and to MAXALT-MLT Orally Disintegrating Tablets.

Tell your doctor about your symptoms. Your doctor will decide if you have migraine. Use MAXALT only for a migraine attack. MAXALT should not be used to treat headaches that might be caused by other, more serious conditions.

You will find more information about migraine at the end of this leaflet.

How should I take MAXALT?

Your doctor has prescribed either a 5-mg or 10-mg dosage of MAXALT or MAXALT-MLT for your migraine attack. When you have a migraine headache, take your medication as directed by your doctor.

MAXALT Tablets

If you are using MAXALT Tablets, swallow the tablet whole with liquid.

MAXALT-MLT Orally Disintegrating Tablets

If you are using MAXALT-MLT, leave the orally disintegrating tablet in its package until you are ready to take it. Remove the blister from the foil pouch. Do not push the tablet through the blister; rather, peel open the blister pack with dry hands and place the tablet on your tongue. The tablet will dissolve rapidly and be swallowed with your saliva. No liquid is needed to take the orally disintegrating tablet.

If your headache comes back after your initial dose, a second dose may be taken anytime after 2 hours of administering the first dose. For any attack where you have no response to the first dose, do not take a second dose without first consulting with your doctor. Do not take more than 30 mg of MAXALT in a 24-hour period (for example, do not take more than three 10-mg tablets in a 24-hour period).

If you are receiving propranolol, you should use the 5-mg dose of MAXALT or MAXALT-MLT, up to a maximum of 3 doses (15 mg total) in a 24-hour period.

If your condition worsens, seek medical attention.

Who should not take MAXALT?

Do not take MAXALT if you:

- have had a serious allergic reaction to MAXALT or any of its ingredients
- have uncontrolled high blood pressure
- have heart disease or history of heart disease
- are currently taking monoamine oxidase (MAO) inhibitors [The brands listed are the trademarks of their respective owners and are not trademarks of Merck Sharp & Dohme Corp., a subsidiary of Merck & Co., Inc.] such as phenelzine sulfate (NARDIL®) or tranylcypromine sulfate (PARNATE®) for mental depression, or have taken MAO inhibitors within the last two weeks.

MAXALT should not be used within 24 hours of treatment with another 5-HT1 agonist [The brands listed are the trademarks of their respective owners and are not trademarks of Merck Sharp & Dohme Corp., a subsidiary of Merck & Co., Inc.] such as sumatriptan (IMITREX®), naratriptan (AMERGE™) or zolmitriptan (ZOMIG™); or ergotamine-type medications such as ergotamine (BELLERGAL-S®, CAFERGOT®, ERGOMAR®, WIGRAINE®), dihydro-ergotamine (D.H.E. 45®), or methysergide (SANSERT®).

What should I tell my doctor before and during treatment with MAXALT?

Tell your doctor:

- about any past or present medical problems
- about any history of high blood pressure, chest pain, shortness of breath, heart disease, or stroke
- about any risk factors for heart disease or blood vessel disease
  - high blood pressure or diabetes
  - high cholesterol
  - obesity
  - smoking
  - family history of heart disease or blood vessel disease
  - post menopausal
  - male over 40
- about any allergies you have or have had
- if you are pregnant or plan to become pregnant
- if you are breast-feeding or plan to breast-feed
- about all drugs you are taking or plan to take, including those obtained without a prescription, and those you normally take for a migraine.
- if you take selective serotonin reuptake inhibitors (SSRIs) or serotonin norepinephrine reuptake inhibitors (SNRIs), two types of drugs for depression or other disorders. Common SSRIs [The brands listed are the trademarks of their respective owners and are not trademarks of Merck Sharp & Dohme Corp., a subsidiary of Merck & Co., Inc.] are CELEXA® (citalopram HBr), LEXAPRO® (escitalopram oxalate), PAXIL® (paroxetine), PROZAC®/SARAFEM®(fluoxetine), SYMBYAX® (olanzapine/fluoxetine), ZOLOFT® (sertraline), and fluvoxamine. Common SNRIs [The brands listed are the trademarks of their respective owners and are not trademarks of Merck Sharp & Dohme Corp., a subsidiary of Merck & Co., Inc.] are CYMBALTA® (duloxetine) and EFFEXOR® (venlafaxine).

MAXALT-MLT orally disintegrating tablets contain aspartame, a source of phenylalanine.

Phenylketonurics: MAXALT-MLT 5-mg and 10-mg orally disintegrating tablets contain 1.05 and 2.10 mg phenylalanine, respectively.

What if I am pregnant?

Do not use MAXALT if you are pregnant, think you might be pregnant, are trying to become pregnant, or are not using adequate contraception, unless you have discussed this with your doctor.

Can I take MAXALT with other medications [The brands listed are the trademarks of their respective owners and are not trademarks of Merck Sharp & Dohme Corp., a subsidiary of Merck & Co., Inc.] ?

Do not take MAXALT with any other drug in the same class within 24 hours, such as sumatriptan (IMITREX®), naratriptan (AMERGE™) or zolmitriptan (ZOMIG™).

Do not take MAXALT within 24 hours of taking ergotamine-type medications such as ergotamine (BELLERGAL-S®, CAFERGOT®, ERGOMAR®, WIGRAINE®), dihydro-ergotamine (D.H.E. 45®) or methysergide (SANSERT®) to treat your migraine.

Do not take MAXALT when you are taking monoamine oxidase (MAO) inhibitors, such as phenelzine sulfate (NARDIL®) or tranylcypromine sulfate (PARNATE®) for mental depression, or if it has been less than two weeks since you stopped taking an MAO inhibitor.

Ask your doctor for instructions about taking MAXALT if you are now taking propranolol (INDERAL®). (See How should I take MAXALT? section.)

Ask your doctor for instructions about taking MAXALT if you are now taking selective serotonin reuptake inhibitors (SSRIs) or serotonin norepinephrine reuptake inhibitors (SNRIs), two types of drugs for depression or other disorders. (See What should I tell my doctor before and during treatment with MAXALT? section.)

What are the possible side effects of MAXALT?

Like all prescription drugs, MAXALT can cause side effects. In studies, MAXALT was generally well-tolerated. The side effects were usually mild and temporary. The following is not a complete list of side effects reported with MAXALT. Do not rely on this leaflet alone for information about side effects. Ask your doctor to discuss with you the more complete list of side effects.

In studies, the most common side effects reported were:

- dizziness
- sleepiness, tiredness, fatigue
- pain or pressure sensation (e.g., in the chest or throat)

If you experience dizziness, sleepiness, tiredness or fatigue, you should evaluate your ability to perform complex tasks such as driving or operating heavy machinery.

Other, less common side effects reported in studies or general use were related to the:

Heart and blood vessels - Alterations in heartbeat, increased blood pressure and spasm of blood vessels of the extremities including coldness and numbness of the hands or feet.

Muscles - Muscle weakness, stiffness, and spasm; and muscle and bone pain.

Nervous system - Nervousness, decreased mental sharpness, tremor, headache, abnormal sensation, vertigo, sleep disturbance, mood and personality changes, alterations in speech and movement, memory impairment, confusion, dream abnormality and seizure.

Digestive system - Stomach upset, diarrhea, dry mouth, constipation, gas, thirst, acid reflux, difficulty swallowing, changes in appetite, burping and inability of the tongue to move.

Skin - Flushing (redness of the face lasting a short time), hot flashes, sweating, itching, rash, acne and skin reaction to sunlight.

Respiratory - Difficult or rapid breathing, dryness or discomfort of the throat or nose, nosebleed, yawning and sinus disorder, cold-like symptoms, cough, and hiccups.

Special Senses - Visual disturbances, ringing in the ears, ear pain, eye discomfort, swelling or tearing, alterations in hearing and smelling, visual intolerance to light, and bad taste.

Miscellaneous - Allergic reactions including swelling of face, lips, tongue and/or throat which may cause difficulty in breathing and/or swallowing, wheezing, hives, rash, and severe sloughing of the skin. Also chills, heat sensitivity, swelling, bloating, hangover effect, fever, fainting, dizziness on standing up, warm/cold sensations, dehydration and changes in urination and menstruation.

As with other drugs in this class, there have been very rare reports of heart attack and stroke generally occurring in patients with risk factors for heart and blood vessel disease (see What should I tell my doctor before and during treatment with MAXALT?).

Tell your doctor about these or any other symptoms. If the symptoms persist or worsen, seek medical attention promptly. In addition, tell your doctor if you experience any symptoms that suggest an allergic reaction (see Miscellaneous above) after taking MAXALT.

What should I do if I take an overdose?

If you take more medication than you have been told to take, you should contact your doctor, hospital emergency department, or nearest poison control center immediately.

What is migraine and how does it differ from other headaches?

Migraine is an intense, throbbing, typically one-sided headache that often includes nausea, vomiting, sensitivity to light, and sensitivity to sound. According to many migraine sufferers, the pain and symptoms from a migraine headache are more intense than the pain and symptoms of a common headache.

Some people may have visual symptoms before the headache, such as flashing lights or wavy lines, called an aura.

Migraine attacks typically last for hours or, rarely, for more than a day, and they can return frequently. The severity and frequency of migraine attacks may vary.

Based on your symptoms, your doctor will decide whether you have migraine.

Who gets migraine?

Migraine headaches tend to occur in members of the same family. Both men and women get migraine, but it is more common in women.

What may trigger a migraine attack?

Certain things are thought to trigger migraine attacks in some people. Some of these triggers are:

- certain foods or beverages (e.g., cheese, chocolate, citrus fruit, caffeine, alcohol)
- stress
- change in a behavior (e.g., under/oversleeping; missing a meal; change in diet)
- hormonal changes in women (e.g., menstruation)

You may be able to prevent migraine attacks or diminish their frequency if you understand what specifically triggers your attacks. Keeping a headache diary may help you identify and monitor the possible migraine triggers you encounter. Once the triggers are identified, you and your doctor can modify your treatment and lifestyle appropriately.

How does MAXALT work during a migraine attack?

Treatment with MAXALT:

1. Reduces swelling of blood vessels surrounding the brain. This swelling results in the headache pain of a migraine attack.
2. Blocks the release of substances from nerve endings that cause more pain and other symptoms of migraine.
3. Interrupts the sending of specific pain signals to your brain.

It is thought that each of these actions contributes to relief of your symptoms by MAXALT.

How should I store MAXALT?

Keep your medicine in a safe place where children cannot reach it. It may be harmful to children. Store your medication away from heat, light, moisture, and at a controlled room temperature 59°-86°F (15°-30°C). If your medication has expired, throw it away as instructed. If your doctor decides to stop your treatment, do not keep any leftover medicine unless your doctor tells you to do so. Throw away your medicine as instructed. Be sure that the discarded tablets are out of the reach of children.

If you are storing MAXALT-MLT, do not remove the blister from the outer aluminum pouch until you are ready to take the medication inside.

This leaflet provides a summary of information about MAXALT. If you have any questions or concerns about either MAXALT or migraine, talk to your doctor. In addition, talk to your pharmacist or other health care provider.

MAXALT Tablets are manufactured for:
Merck Sharp & Dohme Corp., a subsidiary of
MERCK & CO., INC., Whitehouse Station, NJ 08889, USA

By:
MSD, Ltd.
Cramlington, Northumberland, NE23 3JU, UK

MAXALT-MLT Orally Disintegrating Tablets are manufactured for:
Merck Sharp & Dohme Corp., a subsidiary of
MERCK & CO., INC., Whitehouse Station, NJ 08889, USA

By:
Catalent UK Swindon, Zydis Ltd.
Swindon, Wiltshire, SN5 8RU, UK

US Patent No.: 5,298,520

Issued August 2010

9652508

Repackaged by:

REBEL DISTRIBUTORS CORP

Thousand Oaks, CA 91320